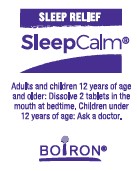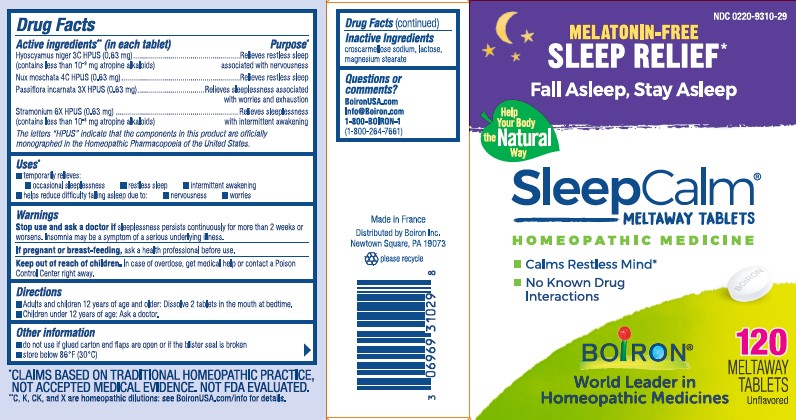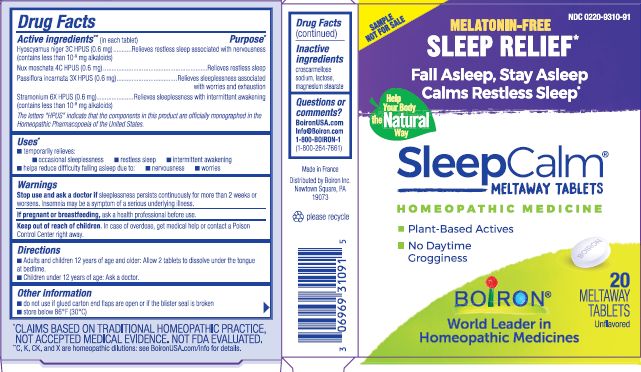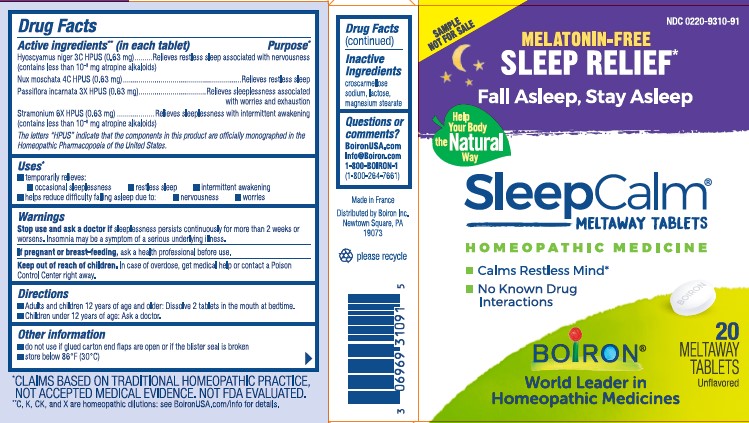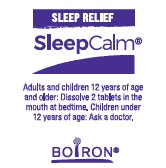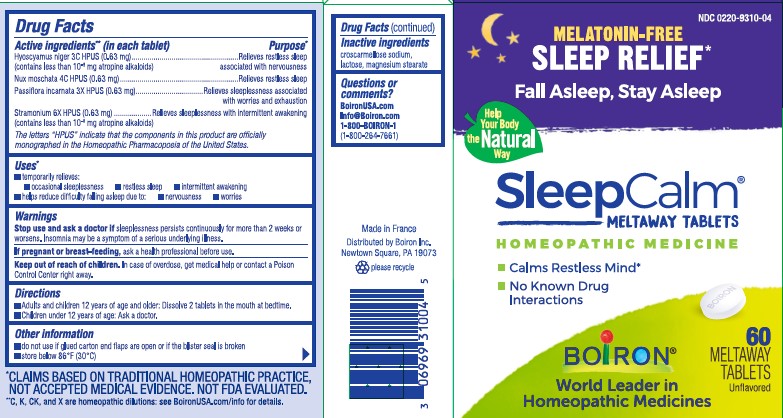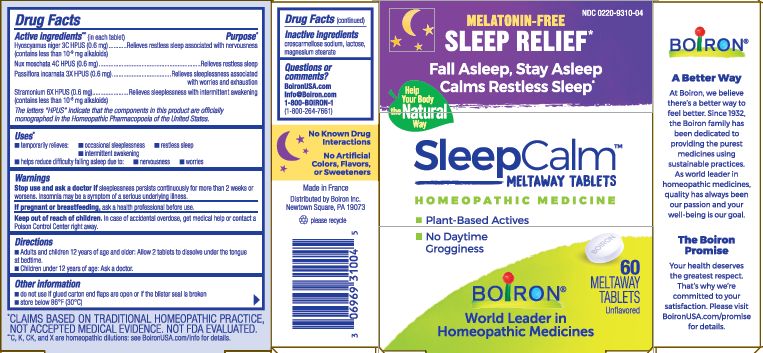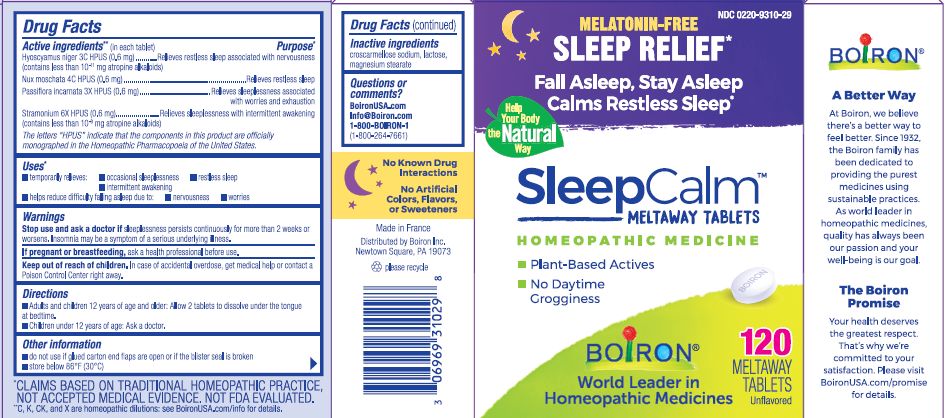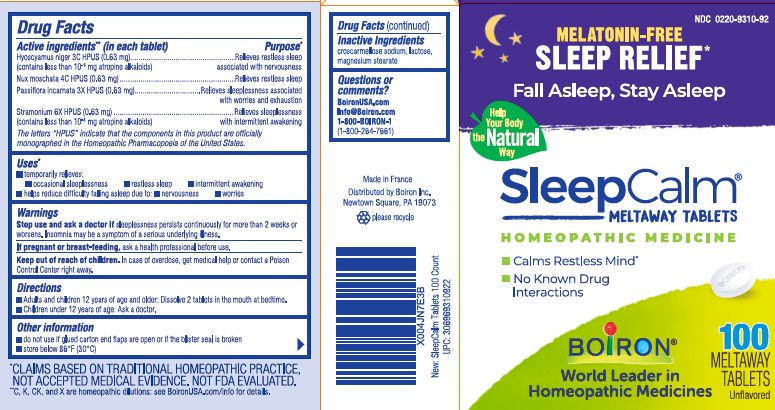 DRUG LABEL: SleepCalm
NDC: 0220-9310 | Form: TABLET
Manufacturer: Laboratoires Boiron
Category: homeopathic | Type: HUMAN OTC DRUG LABEL
Date: 20250321

ACTIVE INGREDIENTS: HYOSCYAMUS NIGER 3 [hp_C]/1 1; PASSIFLORA INCARNATA TOP 3 [hp_X]/1 1; DATURA STRAMONIUM 6 [hp_X]/1 1; NUTMEG 4 [hp_C]/1 1
INACTIVE INGREDIENTS: CROSCARMELLOSE SODIUM; LACTOSE, UNSPECIFIED FORM; MAGNESIUM STEARATE

SleepCalm

Active Ingredients** (in each tablet)

Hyoscyamus niger 3C HPUS (0.63 mg) (contains less than 10^-9 mg alkaloids)
Nux moschata 4C HPUS (0.63 mg)
Passiflora incarnata 3X HPUS (0.63 mg)
Stramonium 6X HPUS (0.63 mg) (contains less than 10-^8 mg alkaloids)

The letters "HPUS" indicate that the components in this product are officially monographed in the Homeopathic Pharmacopoeia of the United States.

Purpose*

Hyoscyamus niger 3C HPUS (0.63 mg) ... Relieves restless sleep associated with nervousness

Nux moschata 4C HPUS (0.63 mg) ... Relieves restless sleep
Passiflora incarnata 3X HPUS (0.63 mg) ... Relieves sleeplessness associated with worries and exhaustion
Stramonium 6X HPUS (0.63 mg) ... Relieves sleeplessness with intermittent awakening

Uses*

temporarily relieves: occasional sleeplessness, restless sleep, intermittent awakening

helps reduce difficulty falling asleep due to: nervousness, worries

Stop use and ask a doctor if sleeplessness persists continuously for more than 2 weeks or worsens. Insomnia may be a symptom of a serious underlying illness.

PREGNANCY OR BREAST FEEDING

If pregnant or breast-feeding, ask a health professional before use.

Keep out of reach of children. In case of overdose, get medical help or contact a Poison Control Center right away.

DOSAGE AND ADMINISTRATION

Adults and children 12 years of age and older: Dissolve 2 tablets in the mouth at bedtime.

Children under 12 of age: Ask a doctor.

do not use if glued carton end flaps are open or if the blister seal is broken

store below 86oF (30oC)

Contains 20 meltaway tablets

Contains 60 meltaway tablets

Contains 100 meltaway tablets

Contains 120 meltaway tablets

*CLAIMS BASED ON TRADITIONAL HOMEOPATHIC PRACTICE NOT ACCEPTED MEDICAL EVIDENCE. NOT FDA EVALUATED.
**C,K,CK, and X are homeopathic dilutions: see BoironUSA.com/info for details.

Calms Restless Mind*

No Known Drug Interactions

Non-habit forming

No artificial sweetners or flavors

Gluten-free

Melatonin-Free

Sleep Relief*

INACTIVE INGREDIENT

croscarmellose sodium, lactose, magnesium stearate

QUESTIONS

BoironUSA.com

Info@boiron.com

1-800-BOIRON-1 (1-800-264-7661)

Made in France

Distributed by Boiron, Inc.

Newtown Square, PA 19073